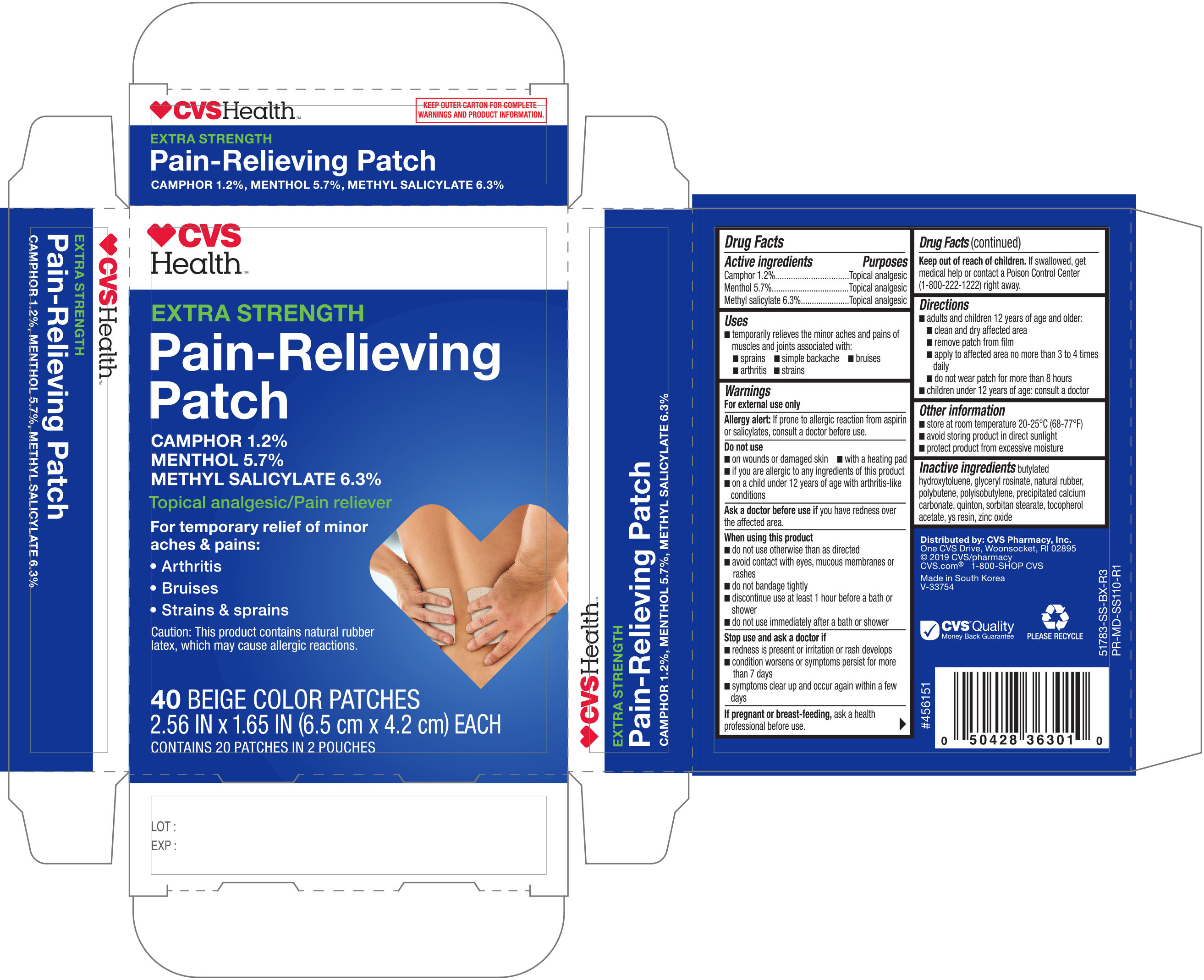 DRUG LABEL: CVS Medicated Pain Relieving
NDC: 59779-551 | Form: PATCH
Manufacturer: CVS Pharmacy, Inc.
Category: otc | Type: HUMAN OTC DRUG LABEL
Date: 20190703

ACTIVE INGREDIENTS: CAMPHOR (SYNTHETIC) 28.4 mg/1 1; MENTHOL 131 mg/1 1; METHYL SALICYLATE 144 mg/1 1
INACTIVE INGREDIENTS: BUTYLATED HYDROXYTOLUENE; NATURAL LATEX RUBBER; POLYBUTENE (1400 MW); CALCIUM CARBONATE; .ALPHA.-TOCOPHEROL ACETATE; ZINC OXIDE

CVS Pain Relieving Patch 40ct (51783, 2019)

Active ingredients Purpose

Camphor 1.2%.......................................................Topical Analgesic

Menthol 5.7%.........................................................Topical Analgesic

Menthyl Salicylate 6.3%..........................................Topical Analgesic

PURPOSE

Uses For temporary relief of minor aches and pains of muscles and joints associated with:

- arthritis
- simple backache
- strains
- bruises
- sprains

Warnings For external use only
Allergy alert: if prone to allergic reation from aspirin or salicylates, consult a doctor before use.

Do not use

- on wounds or damaged skin
- with a heating pad
- if you are allergic to any ingredients of this product
- on a child under 12 years of age with arthritis-like conditions

Ask a doctor before use if you have redness over the affected area.

When using this product

- do not use otherwise than directed
- avoid contact with the eyes, mucous membranes or rashes
- do not bandage tightly
- discontinue use at least 1 hour before a bath or shower
- do not use immediately after a bath or shower

Stop use and ask a doctor if

- redness is present or irritation or rash develops
- conditions worsen or symptoms persist for more than 7 days
- symptoms clear up and occur again within a few days

PREGNANCY OR BREAST FEEDING

If pregnant or breast-feeding, ask a health professional before use.

Keep out of reach of children. If swallowed, get medical help or contact a Poison Control Center (1-800-222-1222) right away.

Directions

Adults and children 12 years of age and over:

- Clean and dry affected area
- Remove patch from film
- Apply to affected area not more than 3 to 4 times daily
- do not wear patch for more than 8 hours

Children under 12 years of age: consult a doctor

Other information

- store at room temperature 20-25°C (68-77°F)
- avoid storing product in direct sunlight
- protect product from excessive moisture

Inactive ingredients

butylated hydroxytoluene, glyceryl rosinate, nautral rubber, polybutene, polysobutylene, precipitated calcium carbonate, quinton, sorbitan stearate, tocopherol acetate, YS resin, zinc oxide

DOSAGE AND ADMINISTRATION

Distributed by:

CVS Pharmacy, Inc.

One CVS Drive, Woonsocket, RI 02895

Made in Korea